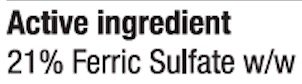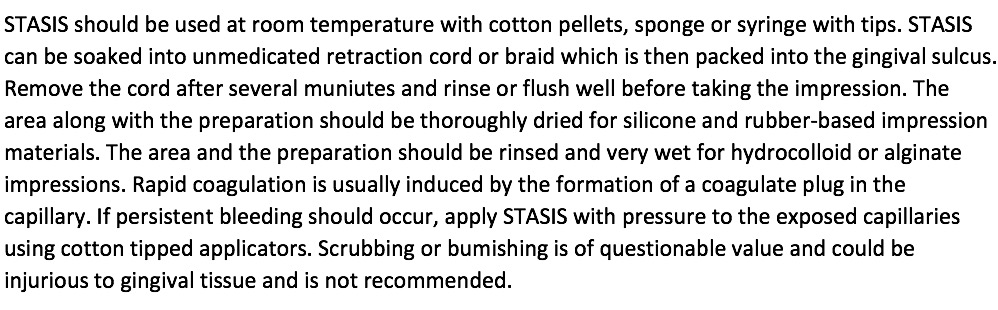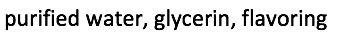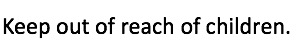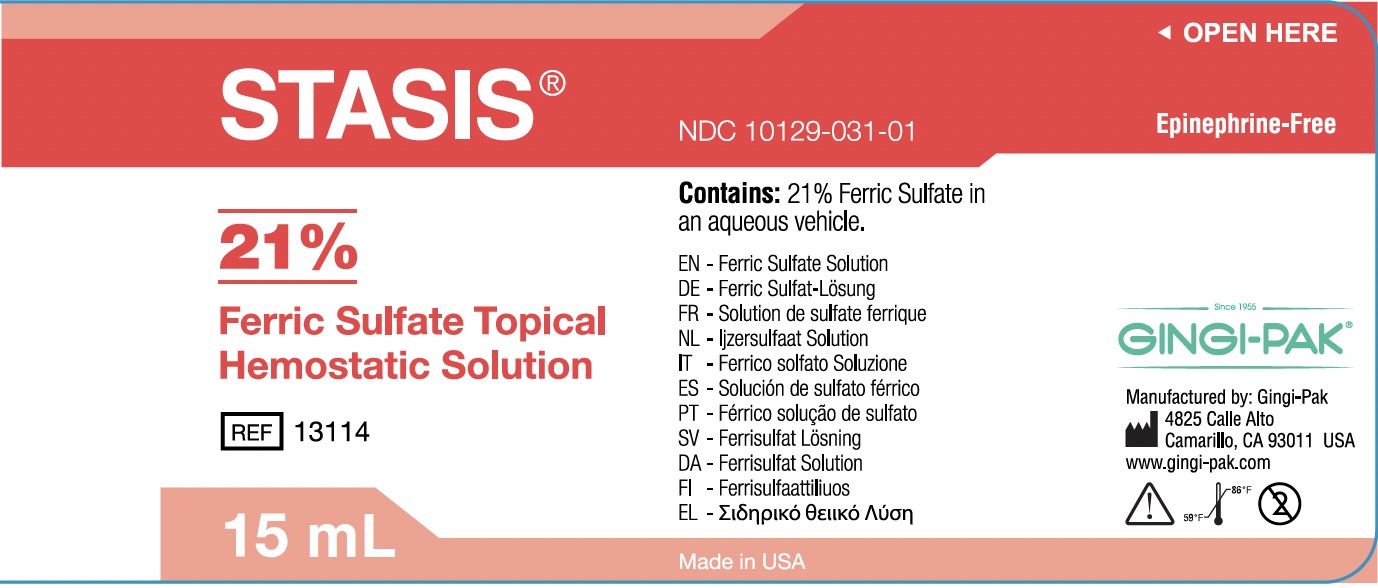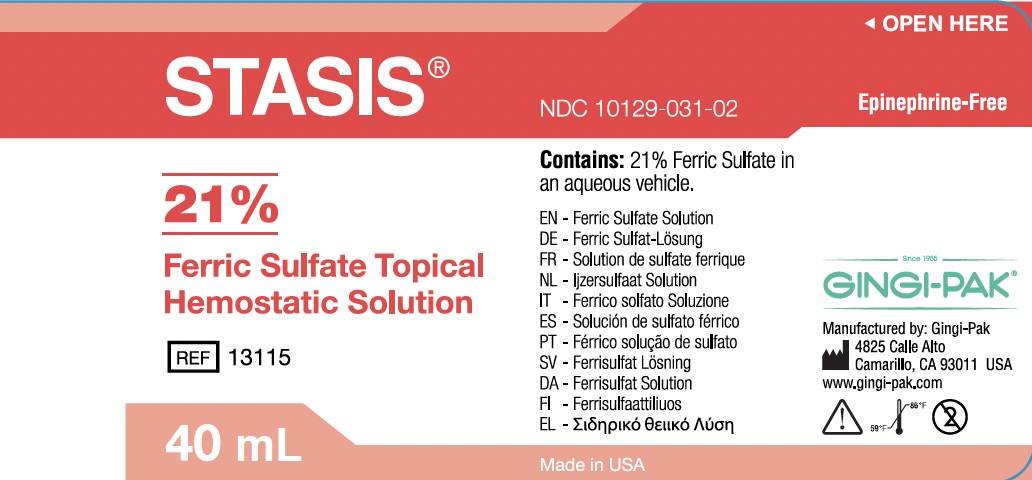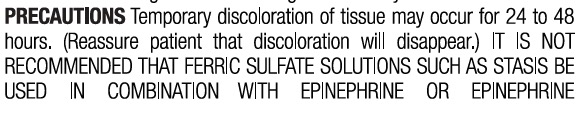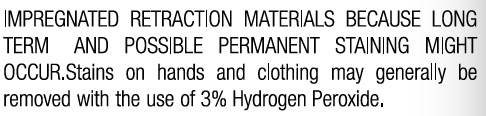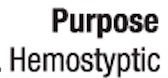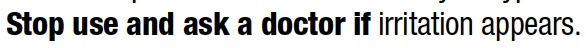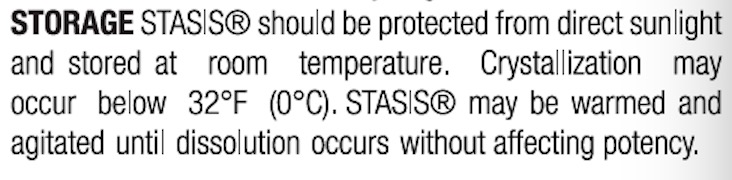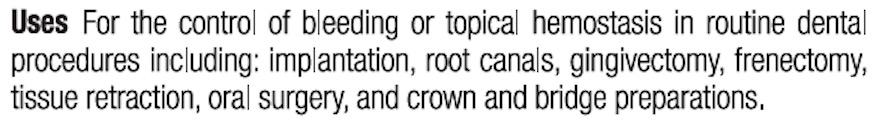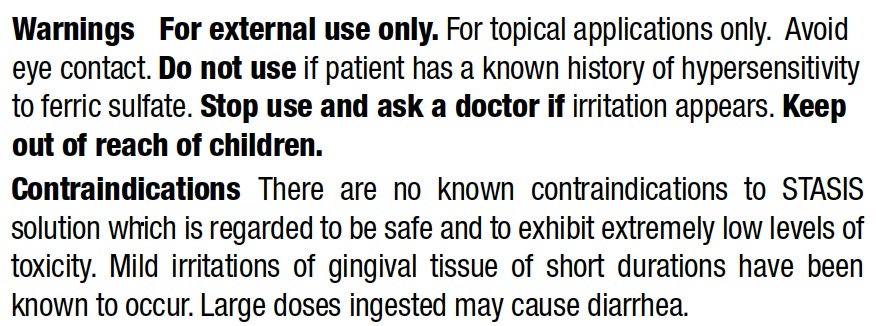 DRUG LABEL: STASIS
NDC: 10129-031 | Form: SOLUTION
Manufacturer: Gingi-Pak a Division of the Belport
Category: otc | Type: HUMAN OTC DRUG LABEL
Date: 20220718

ACTIVE INGREDIENTS: FERRIC SULFATE 3150 mg/15 mL
INACTIVE INGREDIENTS: GLYCERIN 0.45 mL/15 mL

Stasis Solution